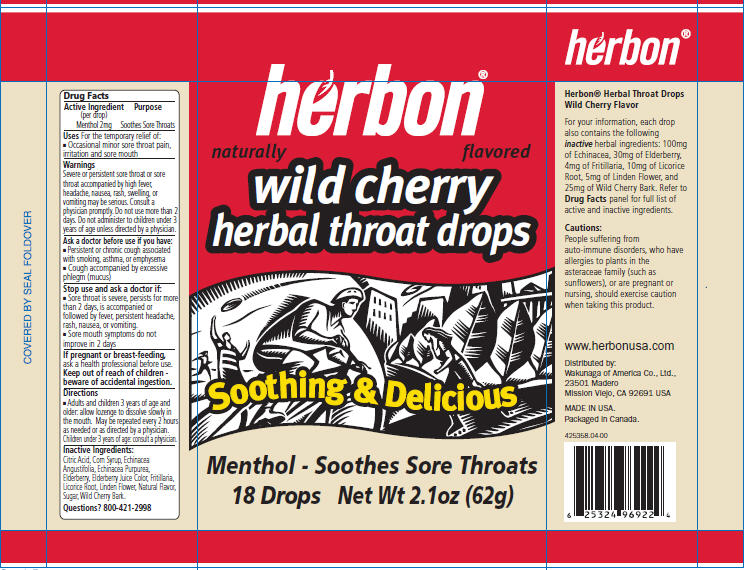 DRUG LABEL: Herbon Wild Cherry
NDC: 44597-5358 | Form: LOZENGE
Manufacturer: Purity Life Division of SunOpta
Category: otc | Type: HUMAN OTC DRUG LABEL
Date: 20091015

ACTIVE INGREDIENTS: Menthol 2 mg/1 1; Echinacea 100 mg/1 1
INACTIVE INGREDIENTS: Citric Acid Monohydrate 2 mg/1 1; Fritillaria; Sucrose; Corn Syrup

Drug Facts

Active Ingredient (per drop)

Menthol 2mg

Purpose

Soothes Sore Throats

Uses

For the temporary relief of:

- Occasional minor sore throat pain, irritation and sore mouth

Warnings

DO NOT USE

Severe or persistent sore throat or sore throat accompanied by high fever, headache, nausea, rash, swelling, or vomiting may be serious. Consult a physician promptly. Do not use more than 2 days. Do not administer to children under 3 years of age unless directed by a physician.

Ask a doctor before use if you have:

- Persistent or chronic cough associated with smoking, asthma, or emphysema
- Cough accompanied by excessive phlegm (mucus)

Stop use and ask a doctor if:

- Sore throat is severe, persists for more than 2 days, is accompanied or followed by fever, persistent headache, rash, nausea, or vomiting.
- Sore mouth symptoms do not improve in 2 days

PREGNANCY OR BREAST FEEDING

If pregnant or breast-feeding, ask a health professional before use.

Keep out of reach of children - beware of accidental ingestion.

Directions

- Adults and children 3 years of age and older: allow lozenge to dissolve slowly in the mouth. May be repeated every 2 hours as needed or as directed by a physician. Children under 3 years of age: consult a physician.

Inactive Ingredients:

Citric Acid, Corn Syrup, Echinacea Angustifolia, Echinacea Purpurea, Elderberry, Elderberry Juice Color, Fritillaria, Licorice Root, Linden Flower, Natural Flavor, Sugar, Wild Cherry Bark.

Questions?

800-421-2998

PRINCIPAL DISPLAY PANEL - 18 Lozenge Bag

herbon®

naturally flavored

wild cherry
herbal throat drops

Soothing & Delicious

Menthol - Soothes Sore Throats
18 Drops Net Wt 2.1oz (62g)